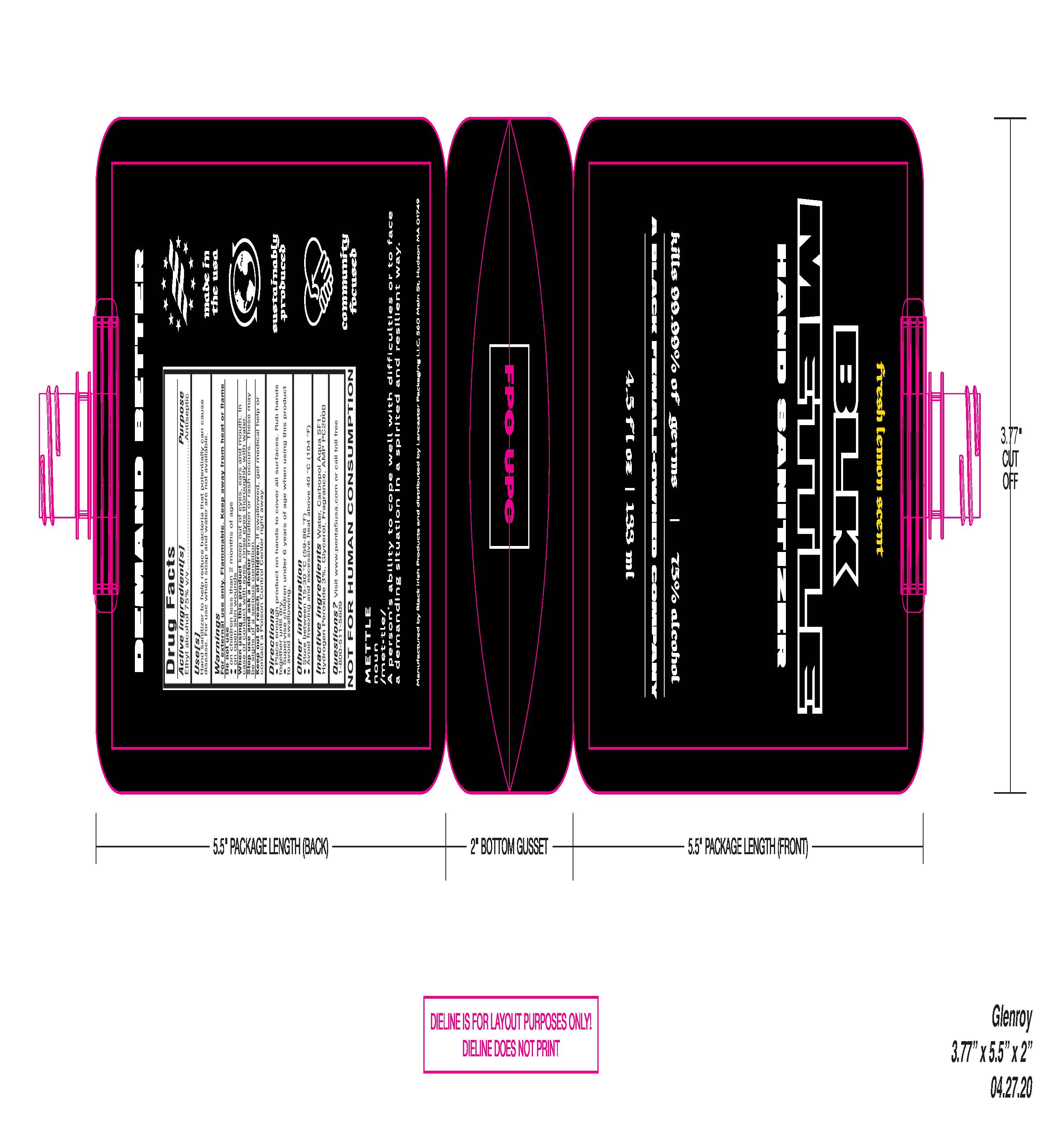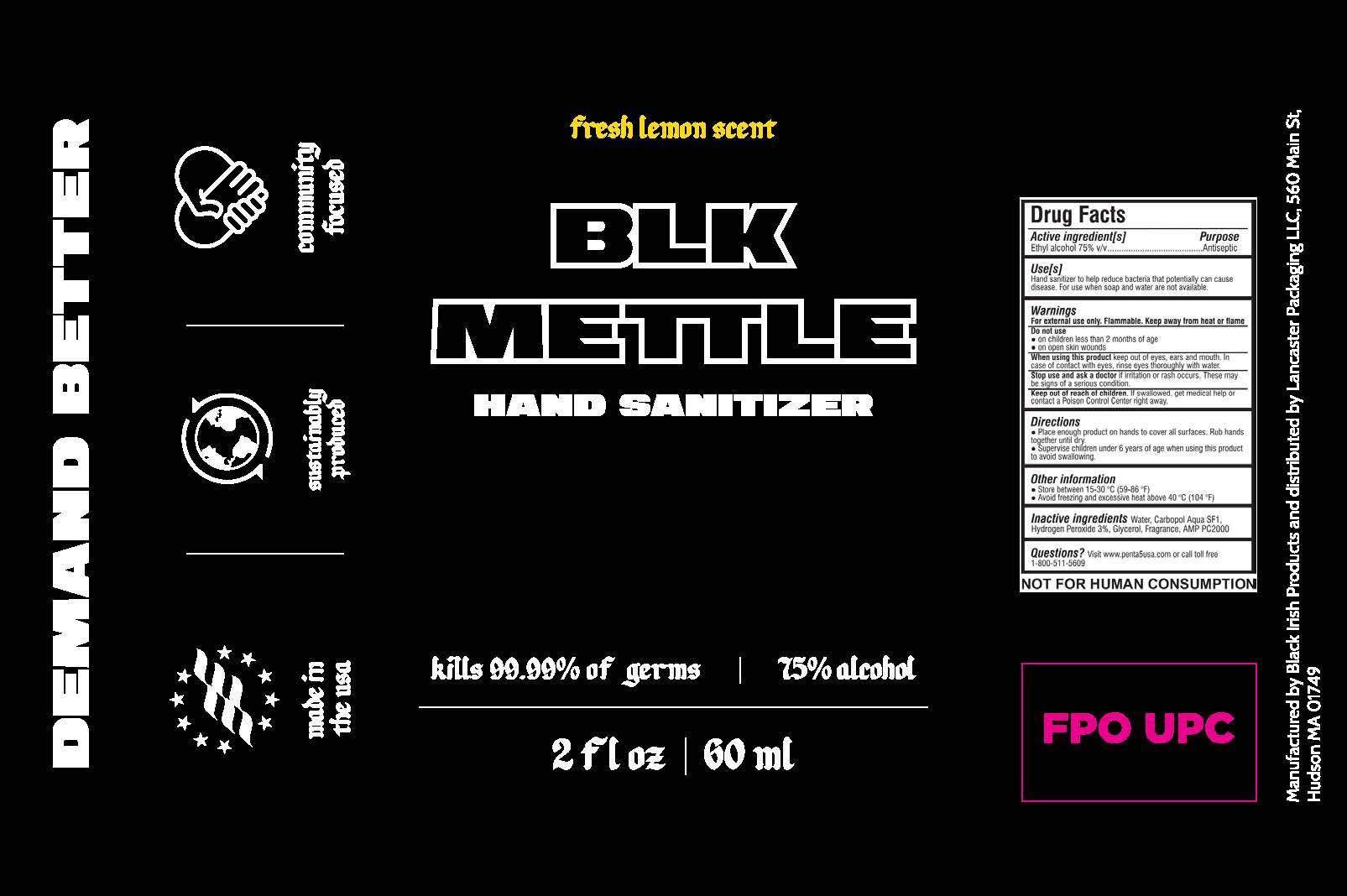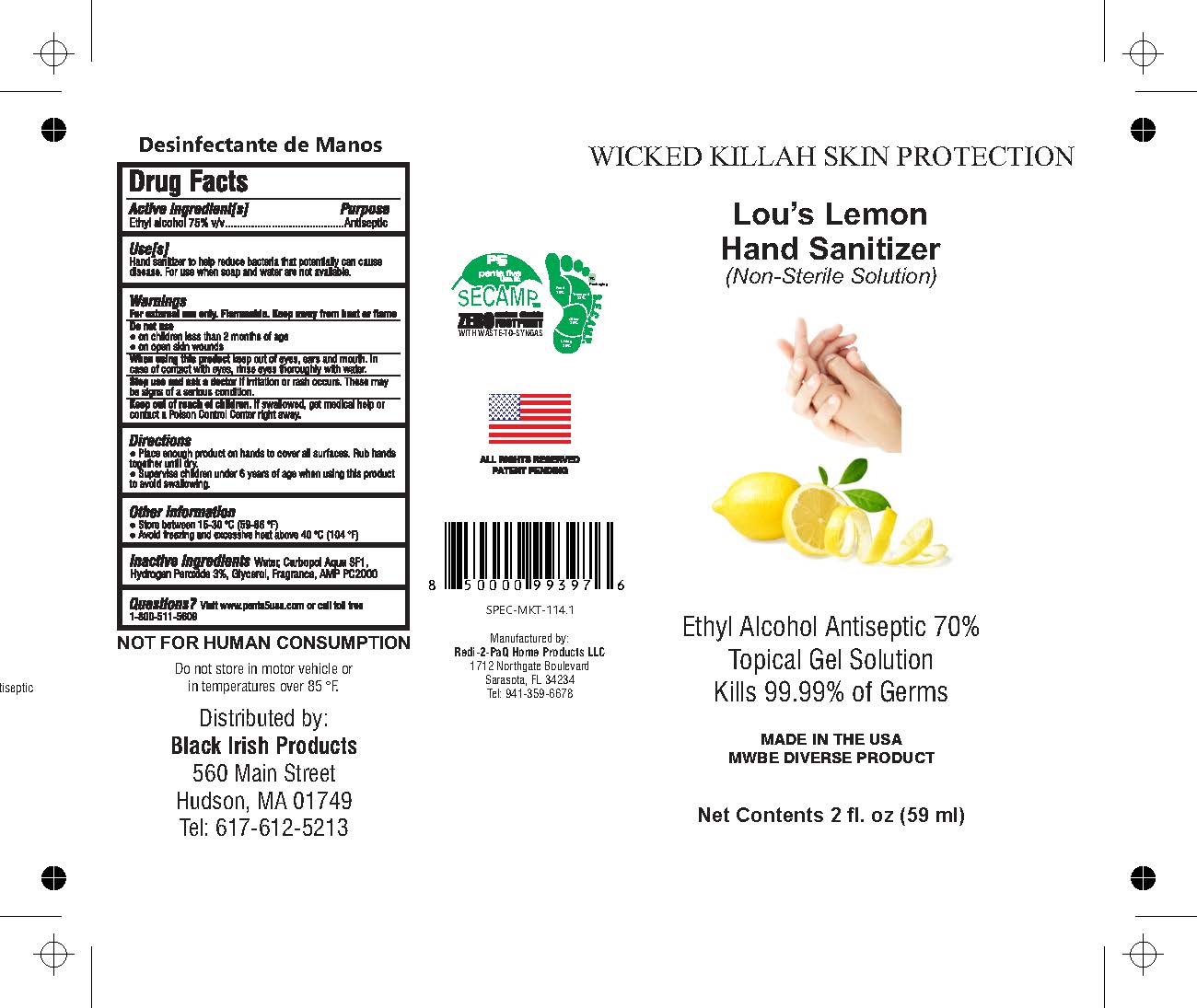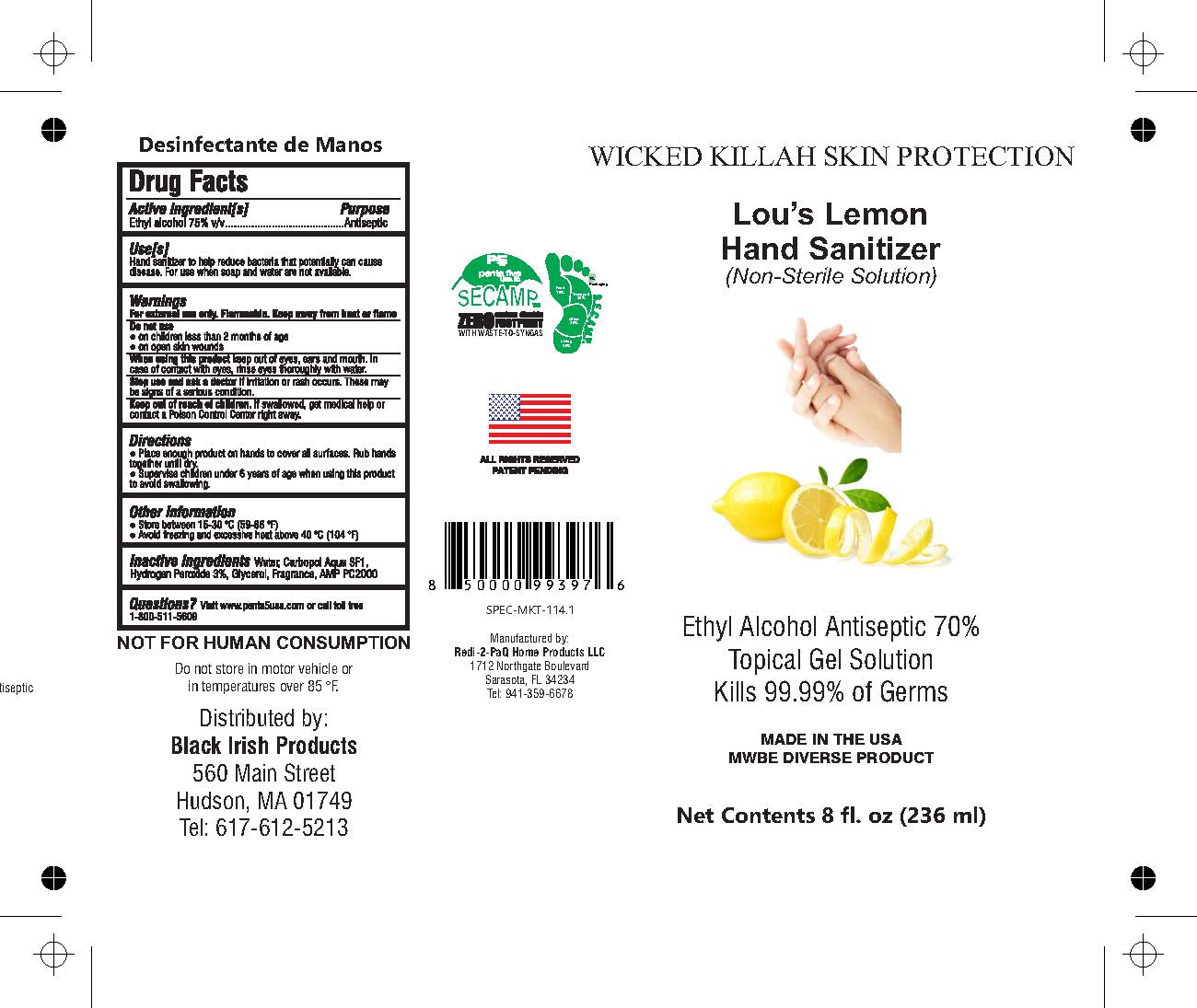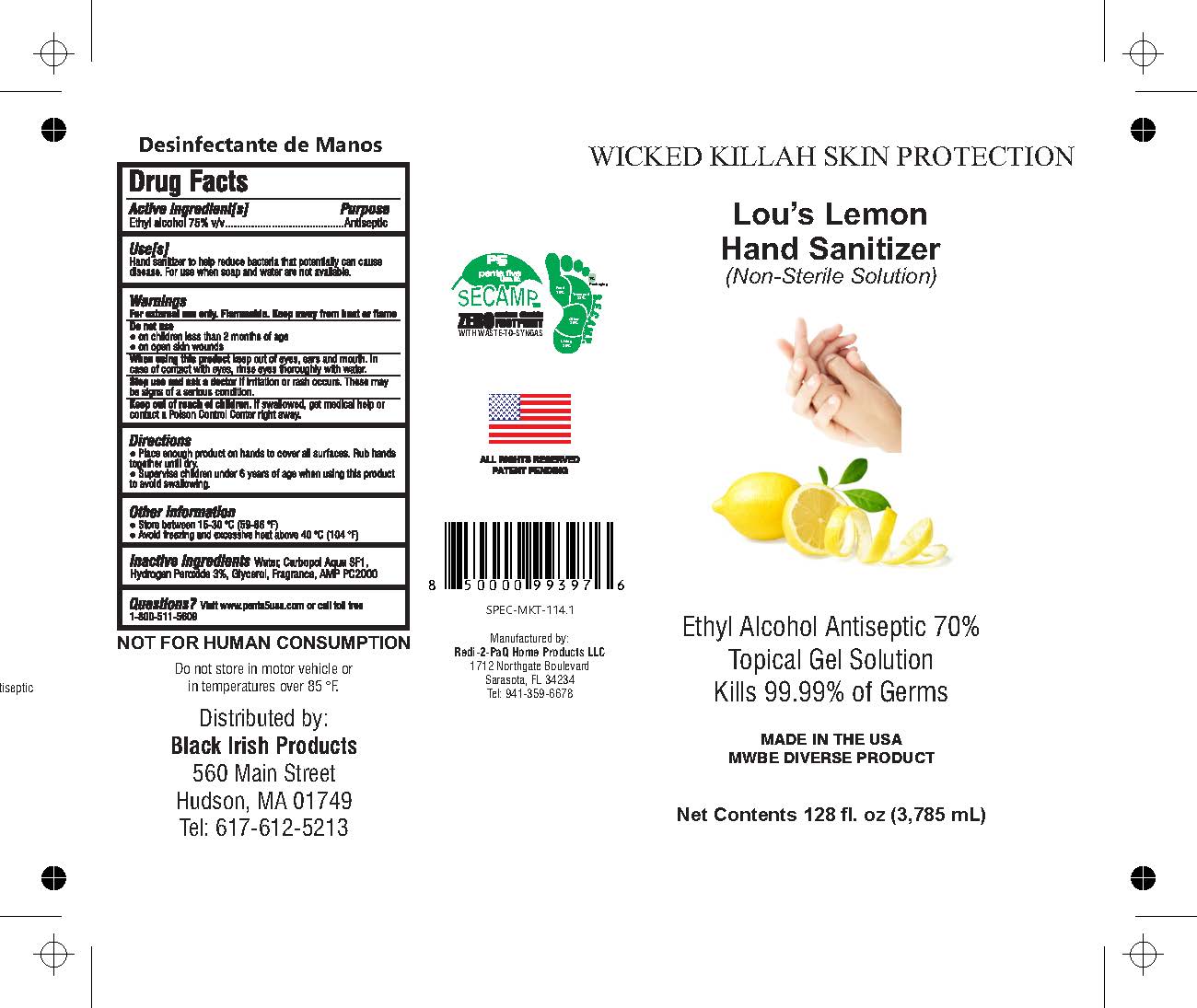 DRUG LABEL: Hand Sanitizer
NDC: 80589-001 | Form: GEL
Manufacturer: Black Irish Products, LLC.
Category: otc | Type: HUMAN OTC DRUG LABEL
Date: 20210325

ACTIVE INGREDIENTS: ALCOHOL 75 mL/100 mL
INACTIVE INGREDIENTS: WATER; CARBOMER COPOLYMER TYPE A; HYDROGEN PEROXIDE; GLYCERIN; FRAGRANCE LEMON ORC2001060; .ALPHA.,.BETA.-METHYLENE ADENOSINE 5'-DIPHOSPHATE

ACTIVE INGREDIENT

Ethyl Alcohol 75% v/v Purpose: Antiseptic

INDICATIONS AND USAGE

WHEN USING

Keep out of eyes, ears, and mouth. In case of contact with the eyes, rinse eyes thoroughly with water.

WHEN USING

- Place enough product on hands to cover all surfaces. Rub hands together until dry.
- Supervise with children under 6 years of age when using this product to avoid swallowing.

WARNINGS

DO NOT USE

- on chilren less then 2 months of age
- on open skin wounds

STOP USE

if irritation or rash occurs. These may be signs of a serious condition.

KEEP OUT OF REACH OF CHILDREN

If swallowed, get medical help or contact a Poison Control Center right away

DOSAGE AND ADMINISTRATION

Apply dime size amount to hands and

PURPOSE

Hand sanitizer to help reuce bacteria that potentially can cause disease. For use when soap and water are not available.

QUESTIONS

Visit penta5usa.com or call toll free 1-800-511-5609

OTHER SAFETY INFORMATION

- Store between 15-30 Degrees C (59-86 F)
- Avoid freexing and excessive heat about 40 C (104 F)

INACTIVE INGREDIENT

Water, Carbopol Aqua SF1, Hydrogen Peroxide 3%, Glycerol, Fragrance, AMP PC2000

PACKAGE LABEL

236 ML, NDC: 80589-001-01

PACKAGE LABEL

59 mL NDC 80589-001-02

PACKAGE LABEL

3785 mL, NDC 80589-001-03

PACKAGE LABEL

60 mL NDC 80589-001-04

PACKAGE LABEL

133 mL NDC 80589-001-05